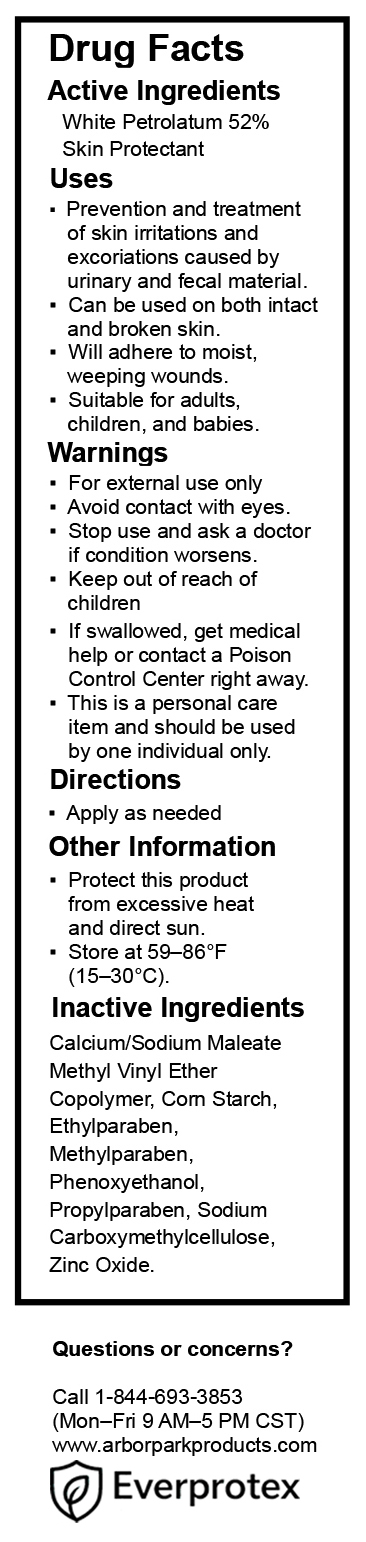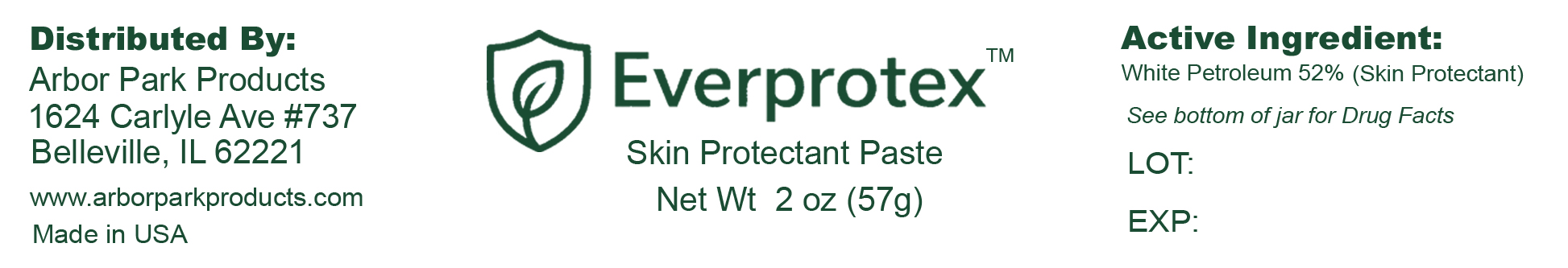 DRUG LABEL: Everprotex
NDC: 87169-001 | Form: PASTE
Manufacturer: Rafael Management Inc
Category: otc | Type: HUMAN OTC DRUG LABEL
Date: 20251010

ACTIVE INGREDIENTS: WHITE PETROLATUM 52 g/100 g
INACTIVE INGREDIENTS: METHYLPARABEN; STARCH, CORN; CARBOXYMETHYLCELLULOSE SODIUM, UNSPECIFIED; CALCIUM/SODIUM MALEATE METHYL VINYL ETHER COPOLYMER (1000000 MW, 1900 MPA.S AT 11%); ETHYLPARABEN; PHENOXYETHANOL; ZINC OXIDE; PROPYLPARABEN

Active Ingredients - See complete Drug Facts labeling (attached image).

White Petrolatum 52% (Skin Protectant).
See attached Drug Facts image for complete labeling.

Purpose - See complete Drug Facts labeling (attached image).

Skin Protectant.
See attached Drug Facts image for complete labeling.

Indications & usage - See complete Drug Facts labeling (attached image).

Prevention and treatment of skin irritations and excoriations caused by urinary and fecal material.
Can be used on both intact and broken skin.
Will adhere to moist, weeping wounds.
Suitable for adults, children, and babies.
See attached Drug Facts image for complete labeling.

Warnings - See complete Drug Facts labeling (attached image).

For external use only.
Avoid contact with eyes.
Stop use and ask a doctor if condition worsens.
This is a personal care item and should be used by one individual only.
See attached Drug Facts image for complete labeling.

Keep out of reach of children - See complete Drug Facts labeling (attached image).

Keep out of reach of children.
If swallowed, get medical help or contact a Poison Control Center right away.
See attached Drug Facts image for complete labeling.

Dosage & Administration - See complete Drug Facts labeling (attached image).

Apply as needed to affected area.
See attached Drug Facts image for complete labeling.

Storage & Handling- See complete Drug Facts labeling (attached image).

Protect this product from excessive heat and direct sun.
Store at 59–86°F (15–30°C).
See attached Drug Facts image for complete labeling.

Inactive Ingredients - See complete Drug Facts labeling (attached image).

Calcium/Sodium Maleate Methyl Vinyl Ether Copolymer, Corn Starch, Ethylparaben, Methylparaben, Phenoxyethanol, Propylparaben, Sodium Carboxymethylcellulose, Zinc Oxide.
See attached Drug Facts image for complete labeling.

Questions- See complete Drug Facts labeling (attached image).

Questions or concerns?
Call 1-844-693-3853 (Mon–Fri 9 AM–5 PM CST)
www.arborparkproducts.com
See attached Drug Facts image for complete labeling.